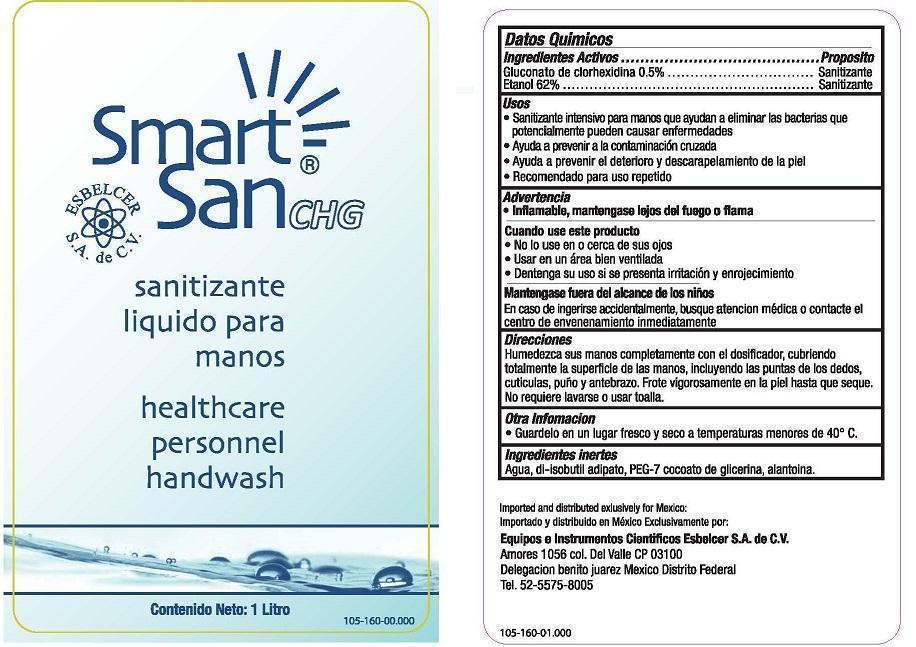 DRUG LABEL: Smart San CHG
NDC: 59900-822 | Form: SOLUTION
Manufacturer: Best Sanitizers, Inc.
Category: otc | Type: HUMAN OTC DRUG LABEL
Date: 20241205

ACTIVE INGREDIENTS: CHLORHEXIDINE GLUCONATE 0.5 g/100 mL; ALCOHOL 6.5 g/100 mL
INACTIVE INGREDIENTS: WATER; DIISOBUTYL ADIPATE; POLYETHYLENE GLYCOL 350; GLYCERYL COCOATE; ALLANTOIN

Smart San CHG 59900-822

Datos Quimicos

Gluconato de clorhexidina 0.5%

Etanol 62%

Proposito

Sanitizante

Usos

- Sanitizante intensivo para manos que ayudan a eliminar las bacterias que potencialmente pueden causar enfermendades
- Ayuda a prevenir a la contaminacion cruzada
- Ayuda a prevenir al deterioro y descarapelamiento de la piel
- Recomendado para uso repetido

Advertencia

- Inflamable, mamtengase lajos del fuago o flama

Cuando use este producto

- No lo use en ocerca de sus ojos
- Usar en un area bien ventilada
- Dentenga su uso si se presenta irriacion y enrojecimiento

Mantegase fuera del alcance de los ninos

En caso de ingerise accidentalmente, busque atencion medica o contacte el centro de envenenamiento inmediatamente

Direcciones

Humendezca sus manos completamente con el dosificador, cubriendo totalmente la superficle de las manos, incluyendo las puntas de los dedos, cuticulas, puno y antebrazo. Frote vigorosamente en la piel hasta que seque. No requiere lavarse o usar toalla.

Otra Infomacion

- Guardelo en un lugar fresco y seco a temperaturas menores de 40° C

Ingredientes inertes

agua, di-isobutil adlpato, PEG-7 cocoato de glicerina, alantoina.

QUESTIONS

Imported and distrubuted exlusively for Mexico:

Importado y distribuido an Mexico Exclusivamente por:

Equipos e Instrumentos Cientificos Esbelcer S.A. de C.V.

Amores 1056 col Del Valle CP 03100

Delegacion benito juares Mexico Distrito Federal

Tel. 52-5575-8005

Principal Display Panel

Smart San CHG

sanitizante liquido para manos

healthcare personnel handwash